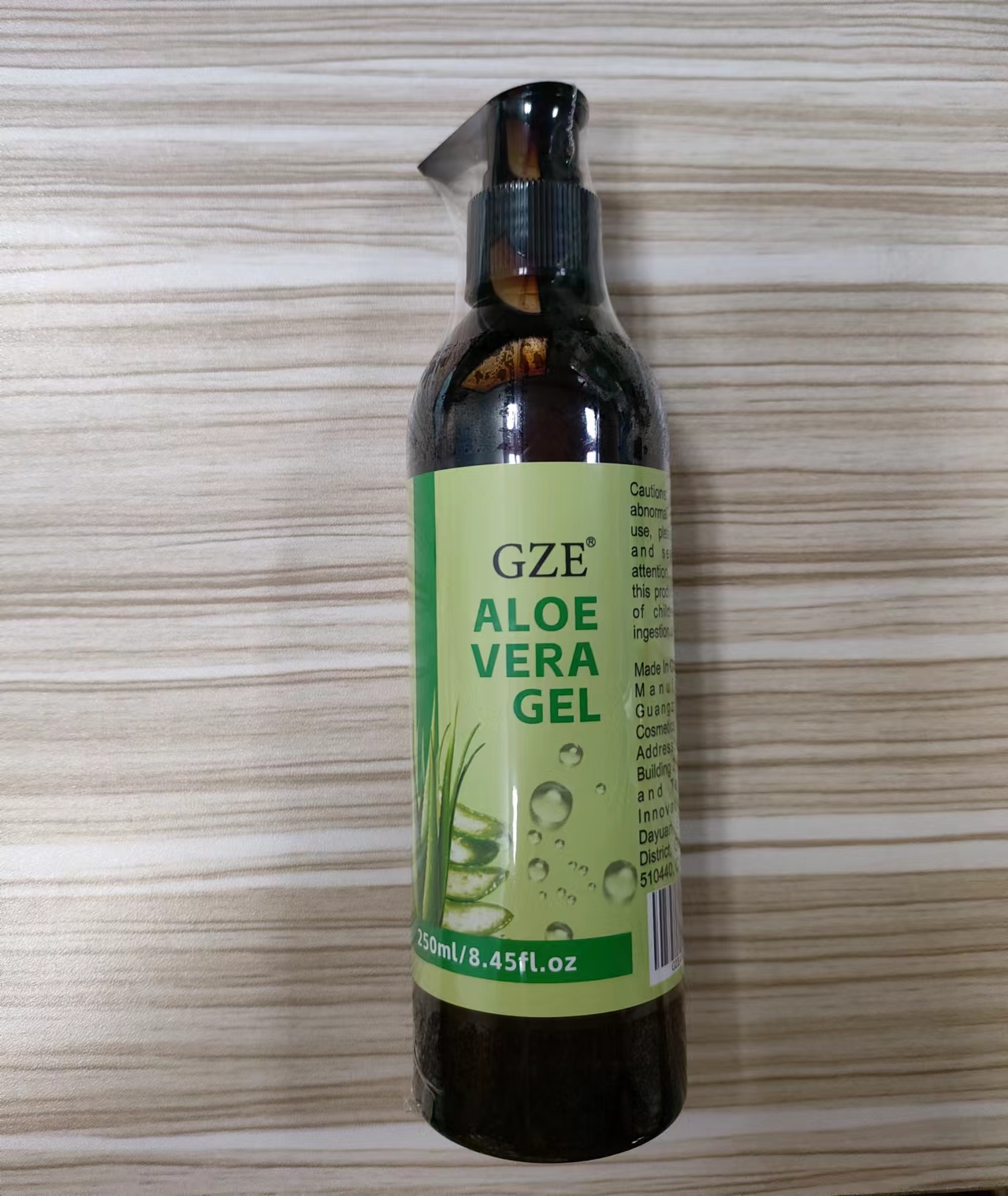 DRUG LABEL: GZE Aloe Vera Gel
NDC: 74458-405 | Form: GEL
Manufacturer: Guangzhou Yilong Cosmetics Co., Ltd
Category: otc | Type: HUMAN OTC DRUG LABEL
Date: 20241113

ACTIVE INGREDIENTS: ALOE BARBADENSIS LEAF JUICE 100 g/100 mL

GZE ALOE VERA GEL

ACTIVE INGREDIENT

Aloe Barbadensis Leaf Juice.

INACTIVE INGREDIENT

none

INDICATIONS AND USAGE

Apply directly to the skin and let it air dry for best results. Use it for healthier skin & hair. Can be added to regular Essential oils, massage oils, daily facial care products, shampoos and hair conditioners.

PURPOSE

Calming and moisturizing.

WARNINGS

For external use only.

Stop use and ask a doctor if rash occurs.

Do not use on damaged or broken skin.

When using this product keep out of eyes. Rinse with water to remove.

DOSAGE AND ADMINISTRATION

Apply directly to the skin and let it air dry for best results. Use it for healthier skin & hair. Can be added to regular Essential oils, massage oils, daily facial care products, shampoos and hair conditioners.